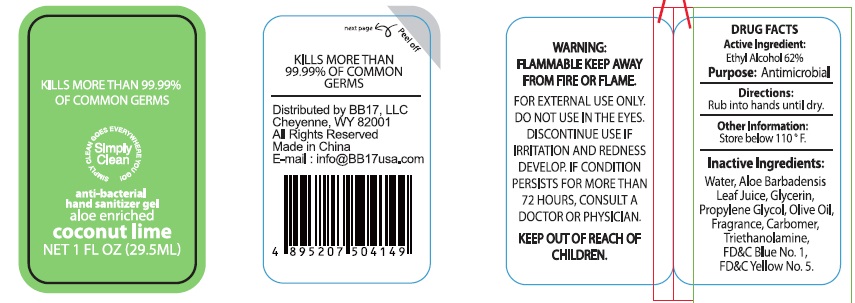 DRUG LABEL: hand sanitizer gel
NDC: 53603-1053 | Form: GEL
Manufacturer: BB17, LLC
Category: otc | Type: HUMAN OTC DRUG LABEL
Date: 20180715

ACTIVE INGREDIENTS: ALCOHOL 62 mL/100 mL
INACTIVE INGREDIENTS: GLYCERIN; PROPYLENE GLYCOL; CARBOMER INTERPOLYMER TYPE A (55000 CPS); TROLAMINE; FD&C BLUE NO. 1; OLIVE OIL; FD&C YELLOW NO. 5; WATER; ALOE VERA LEAF

Active Ingredient:
Ethyl Alcohol 62%

Purpose:
Antimicrobial

WARNING:
FLAMMABLE. KEEP AWAY FROM FIRE OR FLAME. FOR EXTERNAL USE ONLY.DO NOT USE IN THE EYES.

DISCONTINUE USE IF IRRITATION AND REDNESS DEVELOP.
IF CONDITION PERSISTS FOR MORE THAN 72 HOURS, CONSULT A DOCTOR OR PHYSICIAN.

KEEP OUT OF REACH OF CHILDREN.

Directions:
Rub into hands until dry.

INACTIVE INGREDIENT

Water, Aloe barbadenis Leaf Juice, Glycerin,Propylene Glycol, Olive Oil, Fragrance, Carbomer, Triethanolamine, FD&C Blue No.1, FD&C Yellow No.5.

Other Information:
Store below 110 F.

INDICATIONS AND USAGE

KILLS MORE THAN 99.99% OF COMMON GERMS